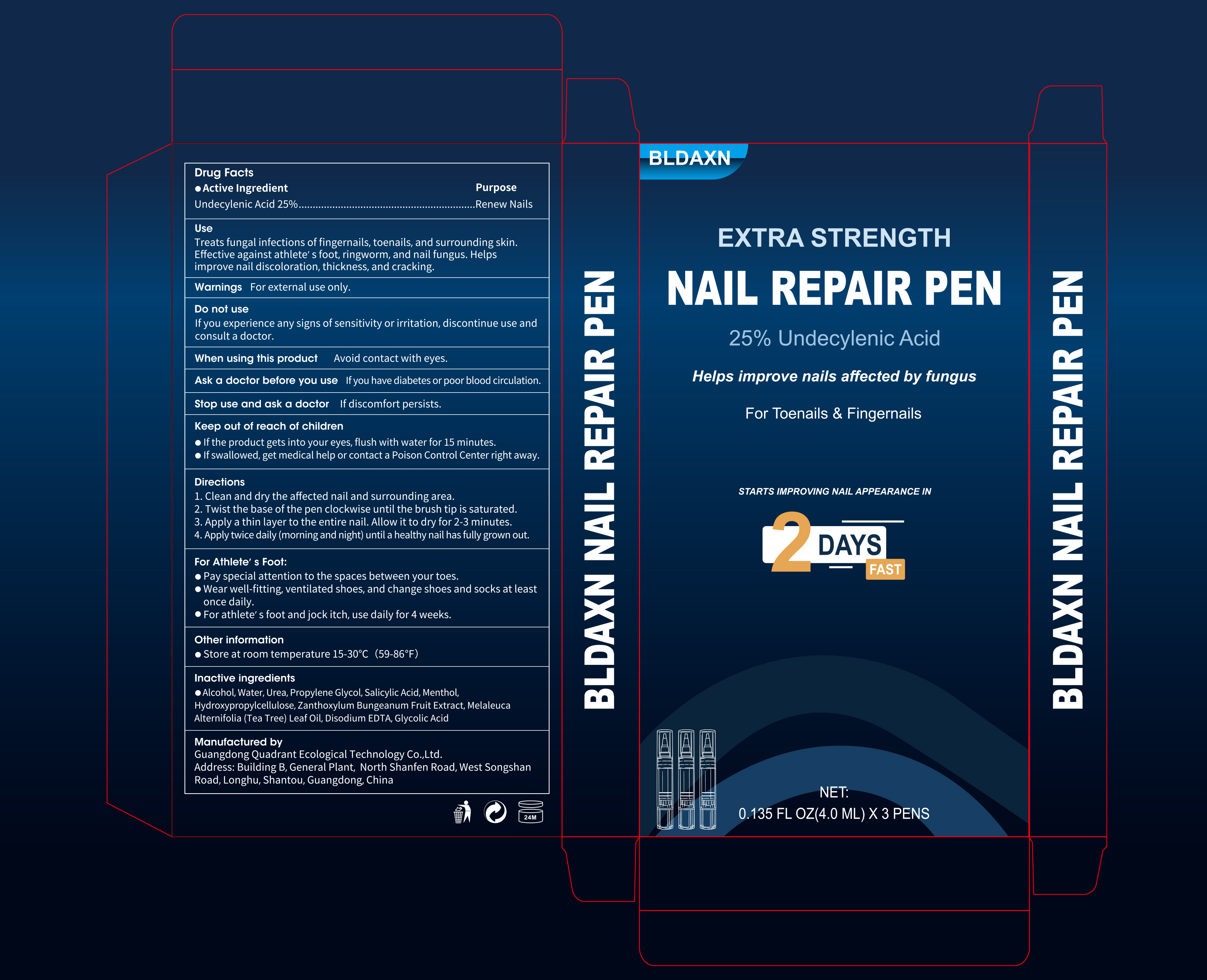 DRUG LABEL: BLDAXN  NAIL REPAIR PEN
NDC: 76986-022 | Form: LIQUID
Manufacturer: Guangdong Quadrant Ecological Technology Co., Ltd.
Category: otc | Type: HUMAN OTC DRUG LABEL
Date: 20260129

ACTIVE INGREDIENTS: UNDECYLENIC ACID 0.25 g/1 mL
INACTIVE INGREDIENTS: ZANTHOXYLUM BUNGEANUM FRUIT; PROPYLENE GLYCOL; EDETATE DISODIUM; WATER; MENTHOL; MELALEUCA ALTERNIFOLIA (TEA TREE) LEAF OIL; ALCOHOL; UREA; HYDROXYPROPYLCELLULOSE; GLYCOLIC ACID; SALICYLIC ACID

76986-022 BLDAXN NAIL REPAIR PEN

ACTIVE INGREDIENT

UNDECYLENIC ACID 25%

PURPOSE

Renew Nails

INDICATIONS AND USAGE

Treats fungal infections offingernails, toenails, and surrounding skin.Effective against athlete's foot, ringworm, and nail fungus. Helps improve nail discoloration, thickness, and cracking.

WARNINGS

For external use only

DO NOT USE

Ifyou experience any signs of sensitivity or irritation, discontinue use and consult a doctor.

When using this product Avoid contact with eyes.
Ask a doctor before you use lfyou have diabetes or poor blood circulation.

Stop use and ask a doctor If discomfort persists

KEEP OUT OF REACH OF CHILDREN

If the product gets into your eyes, flush with water for 15 minutes
Ifswallowed, get medical help or contact a Poison Control Center right away.

DOSAGE AND ADMINISTRATION

1. Clean and dry the affected nail and surrounding area.

2. Twist the base of the pen clockwise until the brush tip is saturated

3. Apply a thin layer to the entire nail. Allow it to dry for 2-3 minutes.

4. Apply twice daily (morning and night) until a healthy nail has fully grown out.
For Athlete's Foot:
Pay special attention to the spaces between your toes.

Wear well-fitting, ventilated shoes, and change shoes and socks at leastonce daily.

For athlete's foot and jock itch, use daily for 4 weeks

INACTIVE INGREDIENT

ALCOHOL
WATER
UREA
PROPYLENE GLYCOL
SALICYLIC ACID
MENTHOL
HYDROXYPROPYLCELLULOSE
ZANTHOXYLUM BUNGEANUM FRUIT EXTRACT
MELALEUCA ALTERNIFOLIA (TEA TREE) LEAF OIL
DISODIUM EDTA
GLYCOLIC ACID